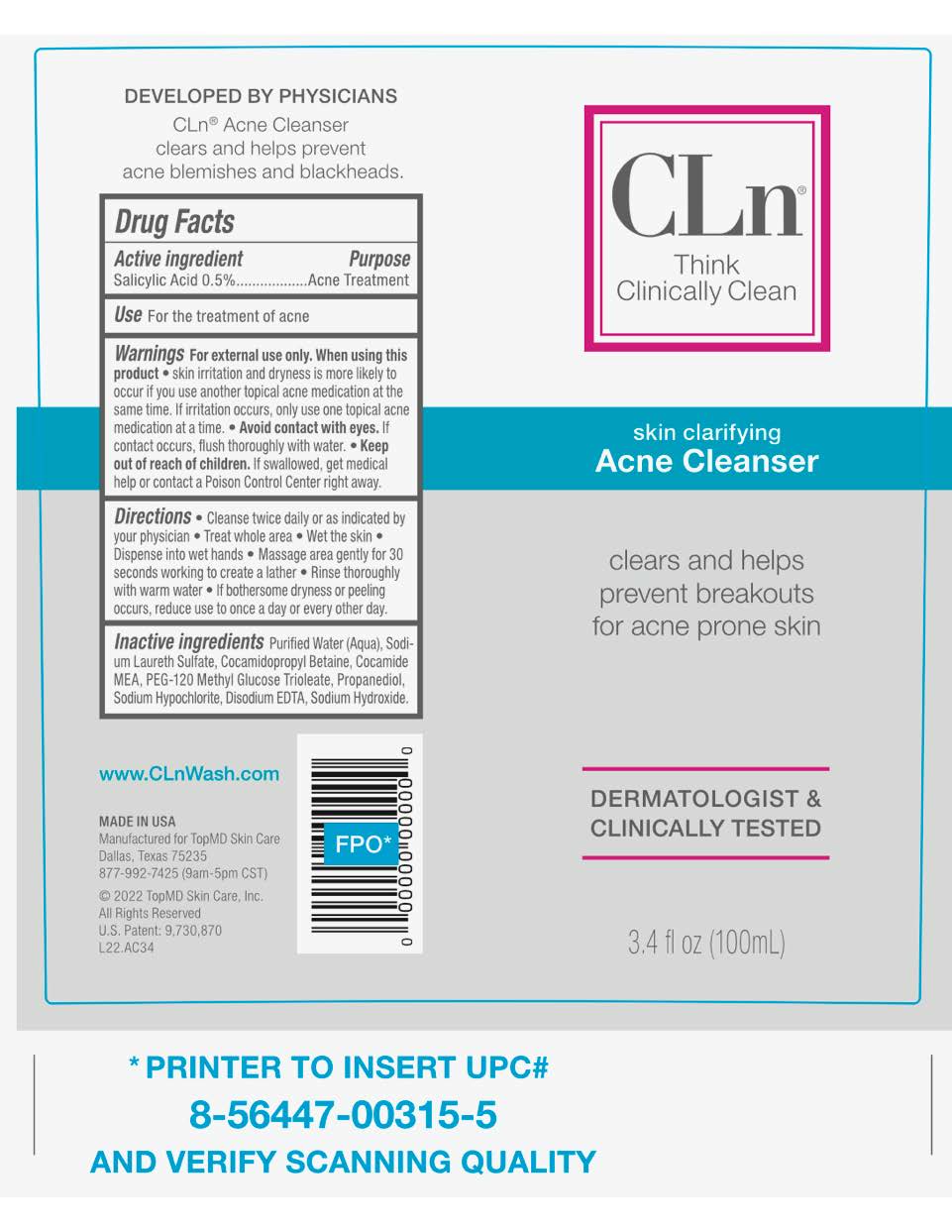 DRUG LABEL: CLN ACNE CLEANSER
NDC: 69530-857 | Form: LIQUID
Manufacturer: TopMD Skin Care, Inc.
Category: otc | Type: HUMAN OTC DRUG LABEL
Date: 20250102

ACTIVE INGREDIENTS: SALICYLIC ACID 5 mg/1 mL
INACTIVE INGREDIENTS: COCO MONOETHANOLAMIDE; SODIUM HYDROXIDE; SODIUM HYPOCHLORITE; EDETATE DISODIUM; WATER; PROPANEDIOL; COCAMIDOPROPYL BETAINE; PEG-120 METHYL GLUCOSE DIOLEATE; SODIUM LAURETH SULFATE

Active Ingredients

Salicylic Acid 0.5%

Purpose

Acne Treatment

Uses

For the treatment of acne

Warnings

For external use only.

When using this product

skin irritation and dryness is more likely to occur if you use another topical acne medication at the same time. If irritation occurs, only use one topical acne medication at a time.

Avoid contact with eyes.

If contact occurs, flush thoroughly with water

Keep out of reach of children.

If swallowed, get medical help or contact a Poison Control Center right away.

Directions

Cleanse twice daily or as indicated by your physician. Treat whole area. Wet the skin. Dispense into wet hands. Massage area gently for 30 seconds working to create a lather. Rinse thoroughly with warm water. If bothersome dryness or peeling occurs, reduce use to once a day or every other day.

Inactive Ingredients

Purified Water (Aqua), Sodium Laureth Sulfate, Cocamidopropyl Betaine, Cocamide MEA, PEG-120 Methyl Glucose Trioleate, Propanediol, Sodium Hypochlorite, Disodium EDTA, Sodium Hydroxide.